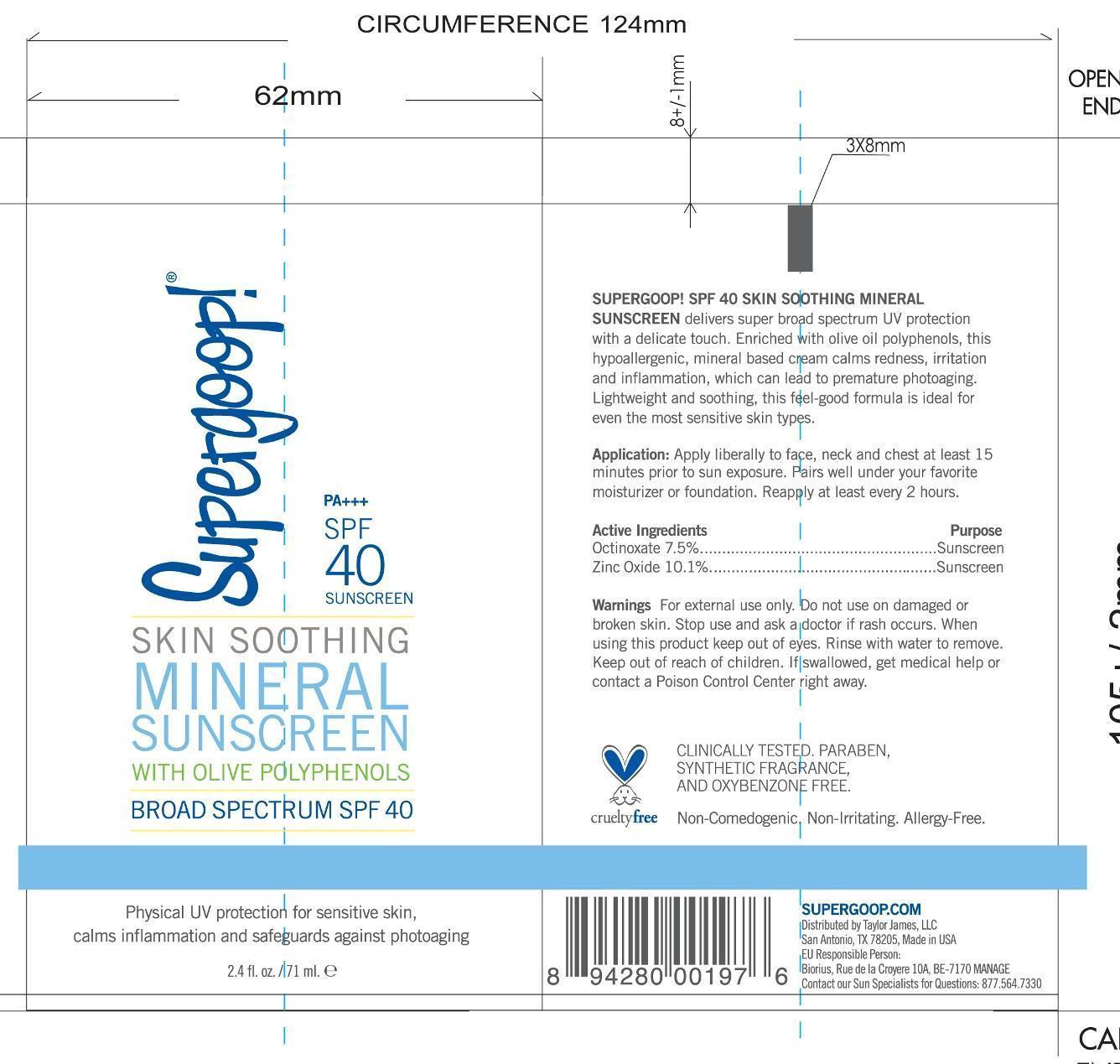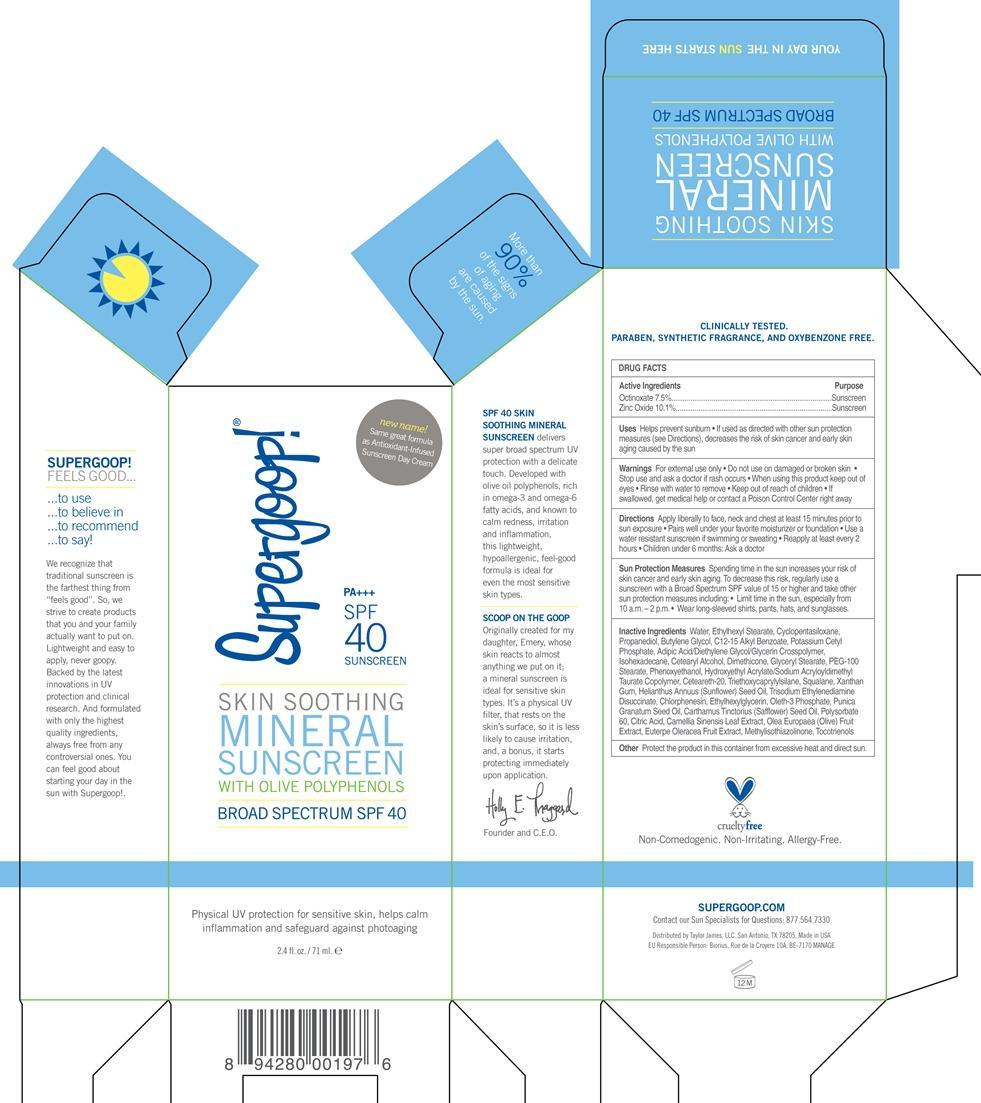 DRUG LABEL: Skin Soothing Mineral Sunscreen Broad Spectrum SPF 40
NDC: 75936-129 | Form: CREAM
Manufacturer: TAYLOR JAMES, LTD.
Category: otc | Type: HUMAN OTC DRUG LABEL
Date: 20181218

ACTIVE INGREDIENTS: OCTINOXATE 7.5 g/100 mL; ZINC OXIDE 10.1 g/100 mL
INACTIVE INGREDIENTS: WATER; ETHYLHEXYL STEARATE; CYCLOMETHICONE 5; PROPANEDIOL; BUTYLENE GLYCOL; ALKYL (C12-15) BENZOATE; POTASSIUM CETYL PHOSPHATE; ISOHEXADECANE; CETOSTEARYL ALCOHOL; DIMETHICONE; GLYCERYL MONOSTEARATE; PEG-100 STEARATE; PHENOXYETHANOL; POLYOXYL 20 CETOSTEARYL ETHER; TRIETHOXYCAPRYLYLSILANE; SQUALANE; XANTHAN GUM; SUNFLOWER OIL; TRISODIUM ETHYLENEDIAMINE DISUCCINATE; CHLORPHENESIN; ETHYLHEXYLGLYCERIN; OLETH-3 PHOSPHATE; POMEGRANATE SEED OIL; SAFFLOWER OIL; POLYSORBATE 60; CITRIC ACID MONOHYDRATE; GREEN TEA LEAF; BLACK OLIVE; ACAI; METHYLISOTHIAZOLINONE; TOCOTRIENOLS

Skin Soothing Mineral Sunscreen SPF 40

Active Ingredients Purpose

Octinoxate 7.5% Sunscreen

Zinc Oxide 10.1% Sunscreen

Uses
· helps prevent sunburn
· If used as directed with other sun protection measures (see Directions),
decreases the risk of skin cancer and early skin aging caused by the sun

· Keep out of reach of children. If swallowed, get medical help or
contact a Poison Control Center right away.

· Stop use and ask a doctor if rash occurs

Warnings

· For external use only
· Do not use on damaged or broken skin
· When using this product keep out of eyes. Rinse with water to remove.

Directions
Apply liberally 15 minutes before sun exposure. Use a water resistant sunscreen if swimming or sweating
-Children under 6 months: Ask a doctor
-Reapply at least every 2 hours
-Sun Protection Measures. Spending time in the sun increases your risk of skin
cancer and early skin aging. To decrease this risk, regularly use a sunscreen
with broad spectrum SPF of 15 or higher and other sun protection measures
including:
· limit time in the sun, especially from 10 a.m. - 2 p.m.
· wear long-sleeve shirts, pants, hats, and sunglasses
· Use a water resistant sunscreen if swimming or sweating

INACTIVE INGREDIENT

Inactive ingredients Water, Ethylhexyl Stearate, Cyclopentasiloxane, Propanediol, Butylene Glycol, C12-15 Alkyl Benzoate, Potassium Cetyl Phosphate, Adipic Acid/Diethylene Glycol/Glycerin Crosspolymer, Isohexadecane, Cetearyl Alcohol, Dimethicone, Glyceryl Stearate, PEG-100 Stearate, Phenoxyethanol, Hydroxyethyl Acrylate/Sodium Acryloyldimethyl Taurate Copolymer, Ceteareth-20, Triethoxycaprylylsilane, Squalane, Xanthan Gum, Helianthus Annuus (sunflower) Seed Oil, Trisodium Ethylenediamine Dissucinate, Chlorphenesin, Ethylhexylglycerin, Oleth-3 Phosphate, Punica Granatum Seed Oil, Carthamus Tinctorius (Safflower) Seed Oil, Polysorbate 60, Citric Acid, Camellia Sinensis Leaf Extract, Olea Europaea (Olive) Fruit extract, Euterpe Oleracaea Fruit Extract, Methylisothiazolinone, Tocotrienols

PACKAGE LABEL

Supergoop Skin Soothing Mineral Sunscreen

with Olive Polyphenols

Broad Spectrum SPF 40

2.4 fl. oz./ 71 mL